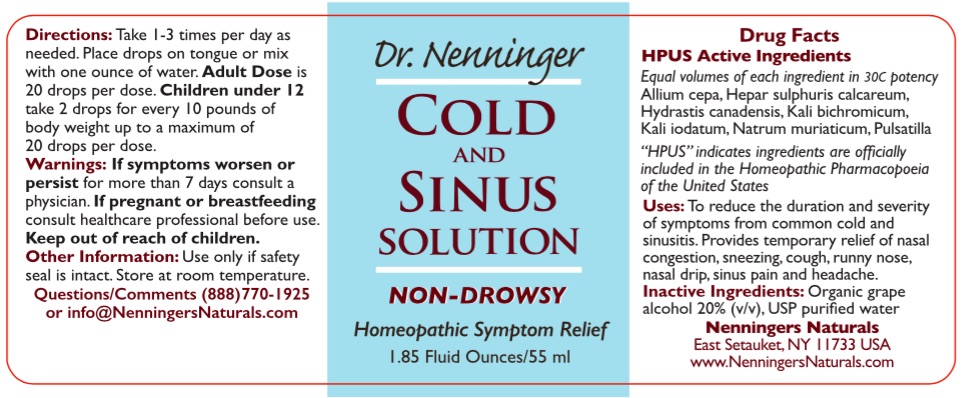 DRUG LABEL: Dr. Nenninger Cold and Sinus Solution
NDC: 42731-062 | Form: LIQUID
Manufacturer: Nenningers Naturals, LLC
Category: homeopathic | Type: HUMAN OTC DRUG LABEL
Date: 20251225

ACTIVE INGREDIENTS: ONION 30 [hp_C]/60 mL; CALCIUM SULFIDE 30 [hp_C]/60 mL; GOLDENSEAL 30 [hp_C]/60 mL; POTASSIUM DICHROMATE 30 [hp_C]/60 mL; POTASSIUM IODIDE 30 [hp_C]/60 mL; SODIUM CHLORIDE 30 [hp_C]/60 mL; ANEMONE PULSATILLA 30 [hp_C]/60 mL
INACTIVE INGREDIENTS: WATER; ALCOHOL

Dr. Nenninger Cold and Sinus Solution

HPUS Active Ingredients Purpose

Equal volumes of each

ingredient in a 30C potency

Allium cepa.....cough, runny nose, sneezing

Hepar sulphuris calcareum.....cough, nasal congestion, sore throat

Hydrastis canadensis......post-nasal drip, nasal congestion, sinusitis

Kali bichromicum......nasal congestion, sinus pain, sneezing

Kali iodatum.....headache, sinus pain

Natrum muriaticum.....runny nose, sneezing

Pulsatilla....cough, earache, nasal congestion

DESCRIPTION

"HPUS" indicates ingredients are included

in the official Homeopathic Pharmacopoeia

of the United States

Uses:

To reduce the duration and severity of symptoms from common cold and sinusitis such as runny nose, sneezing, nasal congestion, post-nasal drip, cough, sore throat, headache, earache and sinus pain.

Warnings:

ASK DOCTOR

If symptoms worsen or persist for more than 7 days consult a physician.

PREGNANCY OR BREAST FEEDING

If pregnant or breastfeeding consult a healthcare professional before use.

Keep out of reach of children.

Directions:

Take 1 to 3 times per day as needed for the symptom relief.

DOSAGE AND ADMINISTRATION

Adult Dose is 20 drops. Children under 12 take 2 drops for every 10 pounds of body weight up to a maximum of 20 drops per dose. Place drops on tongue or mix with 1 oz. of water.

Other Information:

Use only if safety seal is intact. Store at room temperature, away from direct sunlight.

Inactive Ingredients:

Organic grape alcohol 20% v/v, USP purified water

Questions/Comments:

(888) 770-1925 or

info@NenningersNaturals.com

Nenningers Naturals, LLC

East Setauket, NY 11733

PACKAGE LABEL

Dr. Nenninger

COLD

AND

SINUS

SOLUTION

NON-DROWSY

Homeopathic

Symptom Relief

Nenningers Naturals

55 ml